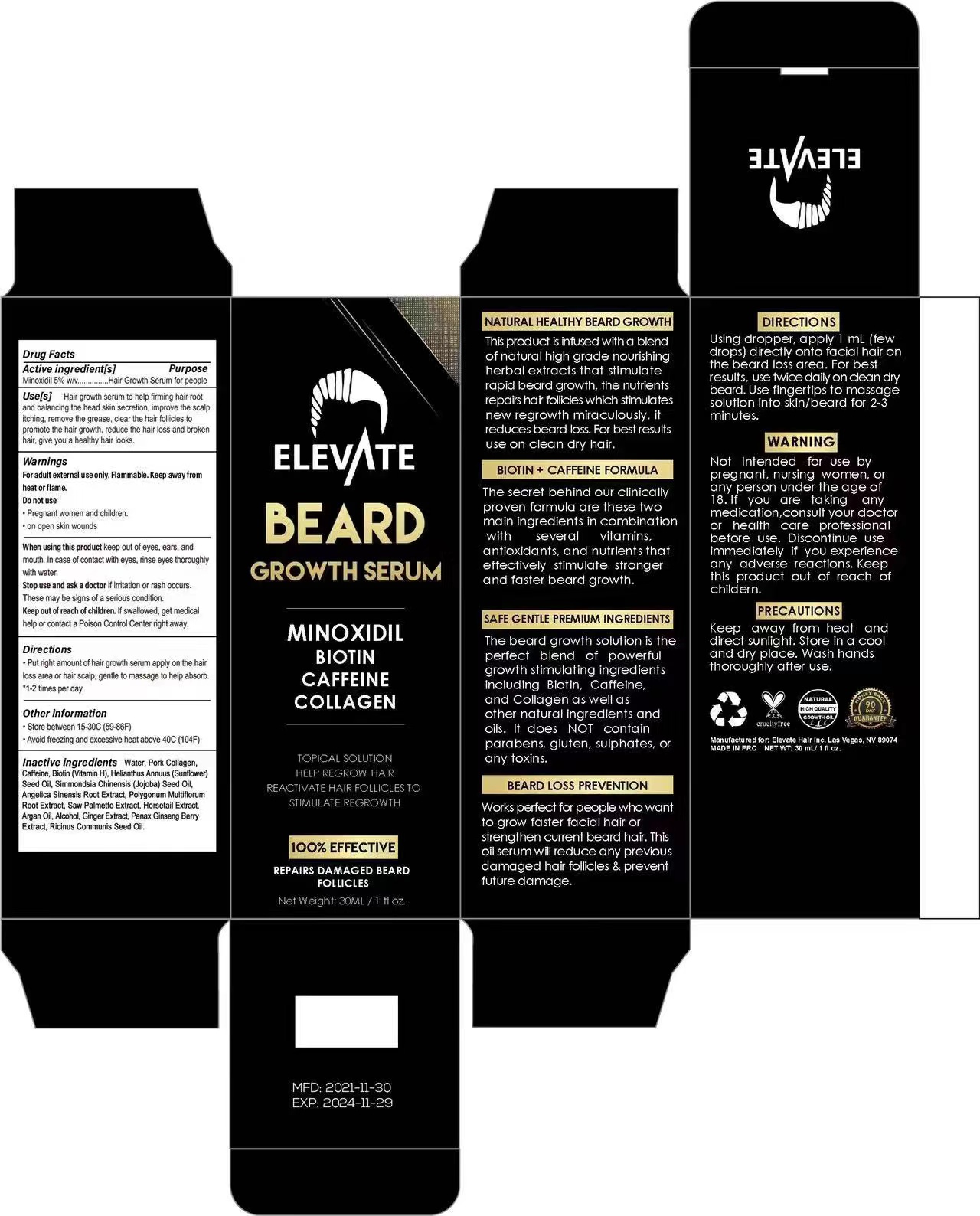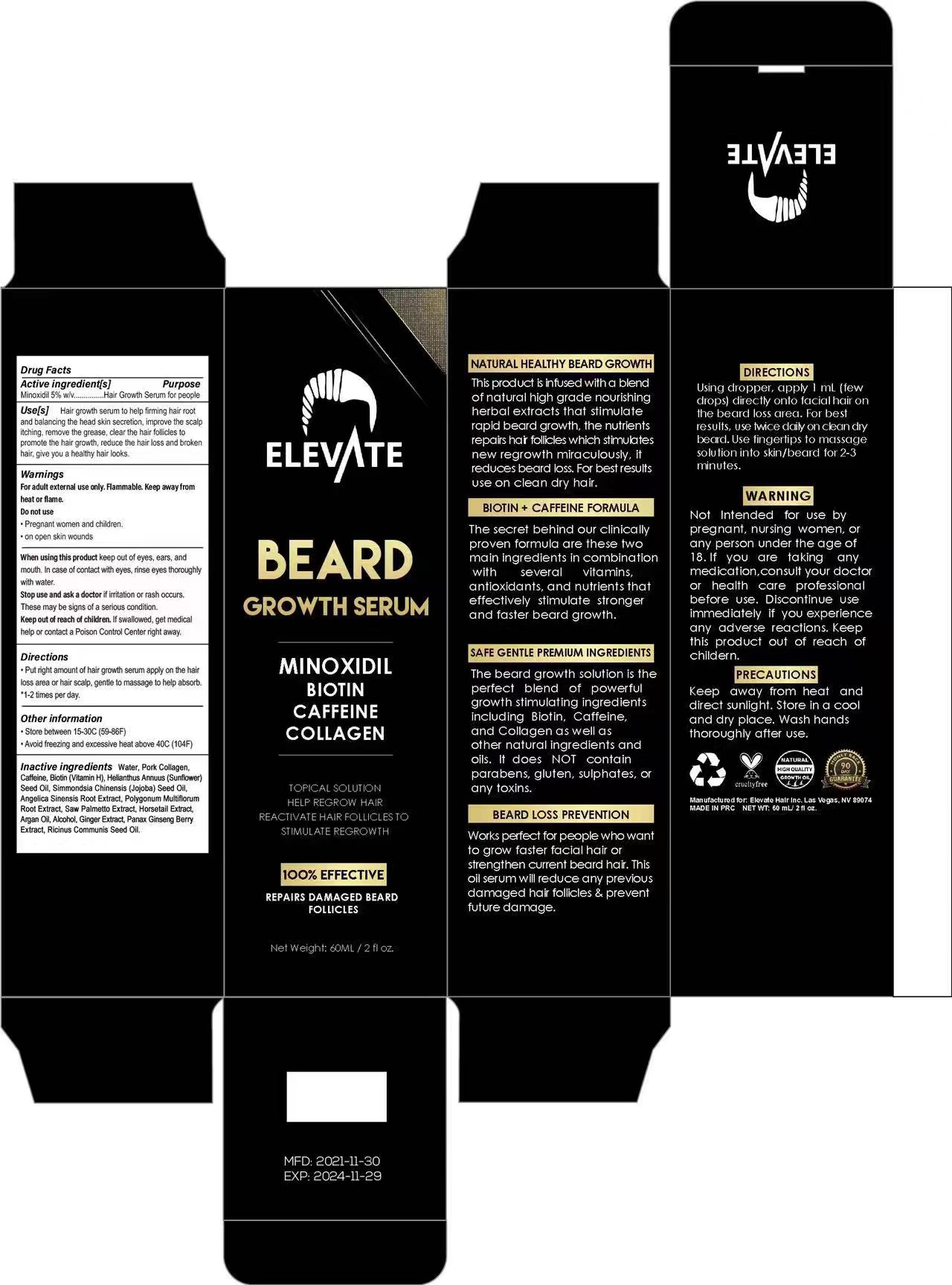 DRUG LABEL: ELEVATE BEARD GROWTH SERUM
NDC: 81653-004 | Form: LIQUID
Manufacturer: Guangzhou Jianyuan Biological Technology.Co.,Ltd
Category: otc | Type: HUMAN OTC DRUG LABEL
Date: 20231219

ACTIVE INGREDIENTS: MINOXIDIL 5 g/100 mL
INACTIVE INGREDIENTS: BIOTIN; WATER; JOJOBA OIL; PORK COLLAGEN; REYNOUTRIA MULTIFLORA ROOT; CAFFEINE; GINGER; CASTOR OIL; SUNFLOWER OIL; ANGELICA SINENSIS ROOT; SAW PALMETTO; ARGAN OIL; ALCOHOL; PANAX GINSENG FRUIT; EQUISETUM HYEMALE

81653-004

ACTIVE INGREDIENT

Minoxidil 5% w/v

PURPOSE

REPAIRS DAMAGED BEARD FOLLICLES
NATURAL HEALTHY BEARD GROWTH

BEARD LOSS PREVENTION

INDICATIONS AND USAGE

Works perfect for people who want to grow faster facial hair or strengthen current beard hair. This oil serum will reduce any previous damaged hair follicles & prevent future damage.

Keep out of reach of children.lf swallowed, get medical help or contact a Poison Control Center right away.

WARNINGS

For adult external use only. Flammable. Keep away fromheat or flame.
Do not use
·Pregnant women and children.
·on open skin wounds

When using this product keep out of eyes, ears, andmouth. In case of contact with eyes, rinse eyes thoroughlywith water.
Stop use and ask a doctor if irritation or rash occurs.These may be signs of a serious condition.

DOSAGE AND ADMINISTRATION

Using dropper, apply 1 mL (few drops) directly onto facial hair on the beard loss area. For best results, use twice daily on clean dry beard.Use fingertips to massage solution into skin/beard for 2-3 minutes.

STORAGE AND HANDLING

- Store between 15-30℃ (59-86℉)
- Avoid freezing and excessive heat above 40℃ (104℉)

lnactive ingredients

Water, Pork Collagen, Caffeine, Biotin (Vitamin H), Helianthus Annuus (Sunflower)Seed Oil, Simmondsia Chinensis (Jojoba) Seed Oil, Angelica Sinensis Root Extract, Polygonum Multiflorum Root Extract, Saw Palmetto Extract, Horsetail Extract, Argan Oil, Alcohol, Ginger Extract, Panax Ginseng Berry Extract, Ricinus Communis Seed Oil

STOP USE

Not lntendedfor use by pregnant, nursing women, any person under the age of 18. lf you are taking any medication, consult your doctor or health care professional before use. Discontinue use immediately if you experience any adverse reactions. Keep this product out of reach of childern.